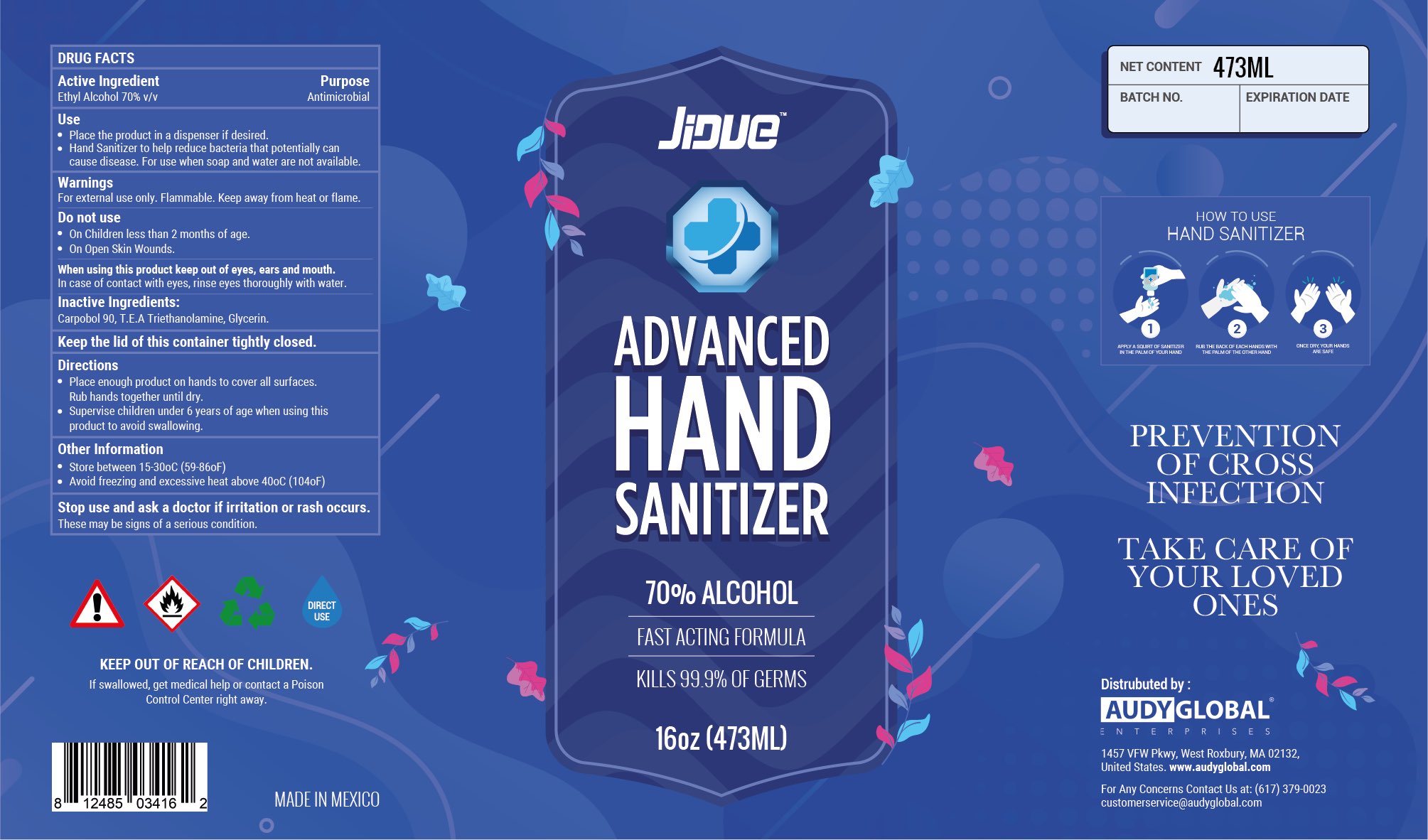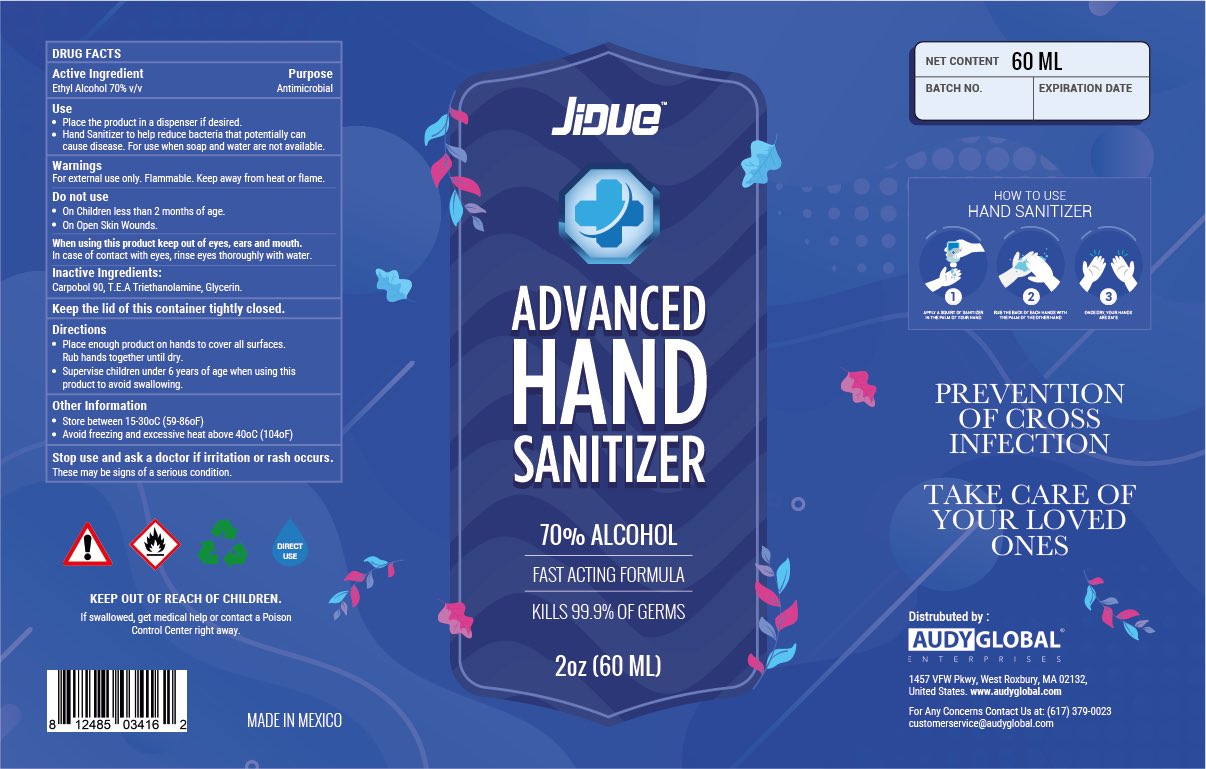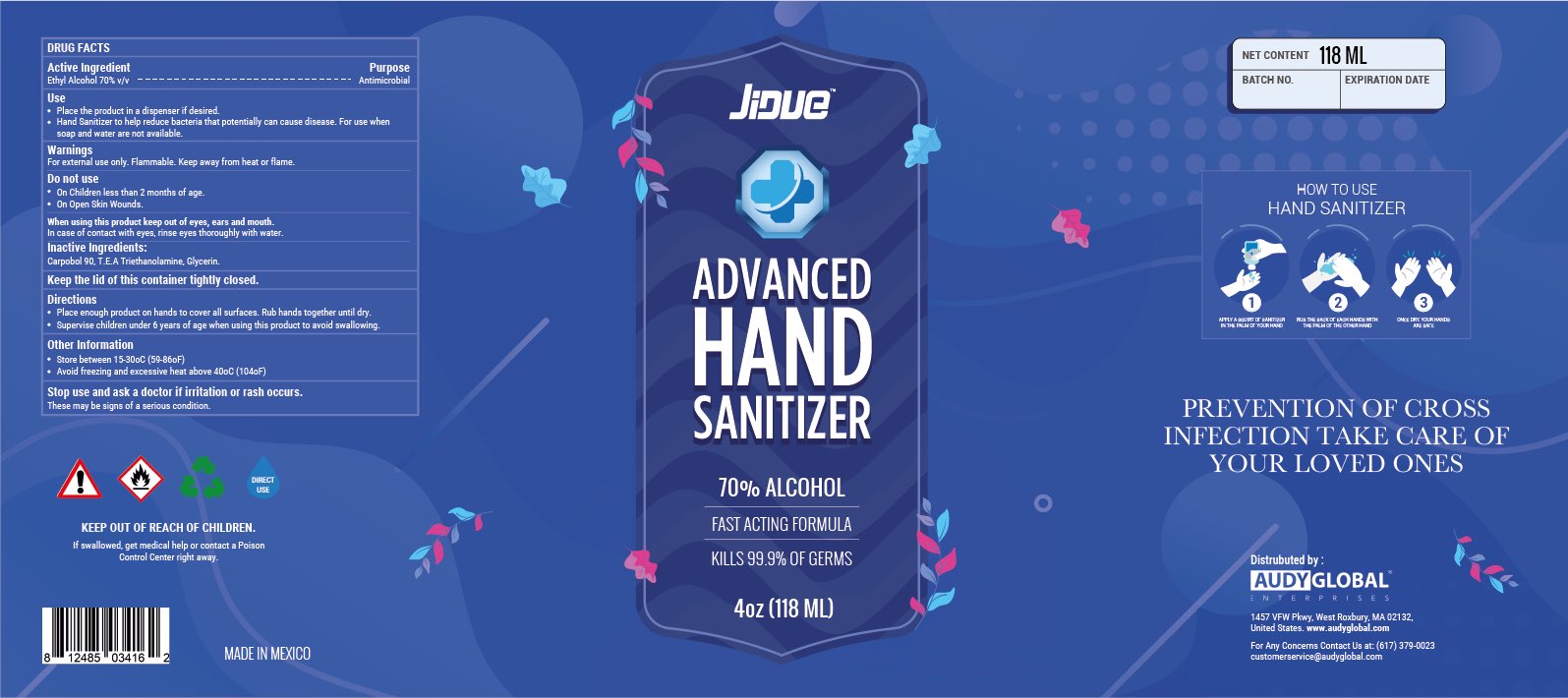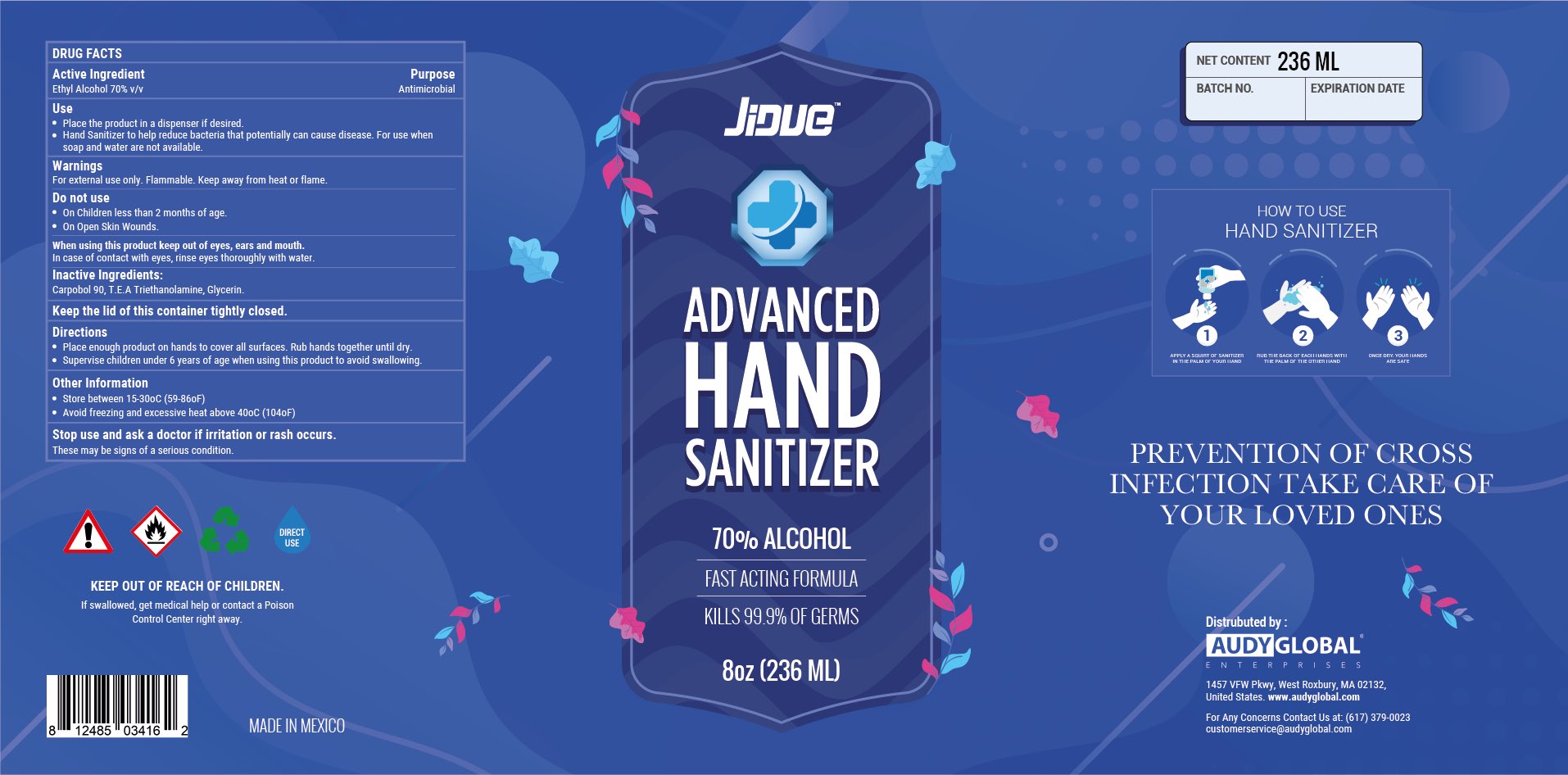 DRUG LABEL: Hand Sanitizer
NDC: 75778-005 | Form: GEL
Manufacturer: Audy Global Enterprises Inc.
Category: otc | Type: HUMAN OTC DRUG LABEL
Date: 20200619

ACTIVE INGREDIENTS: ALCOHOL 70 mL/100 mL
INACTIVE INGREDIENTS: GLYCERIN; TROLAMINE; POLYACRYLIC ACID (800000 MW)

Active Ingredient(s)

Ethyl Alcohol 70%

Purpose

Antimicrobial

Use

Hand Sanitizer to help reduce bacteria that potentially can cause disease. For use when soap and water are not available.

Warnings

For external use only. Flammable. Keep away from heat or flame

Do not use

- in children less than 2 months of age
- on open skin wounds

When using this product keep out of eyes, ears, and mouth. In case of contact with eyes, rinse eyes thoroughly with water.

Stop use and ask a doctor if irritation or rash occurs. These may be signs of a serious condition.

Keep out of reach of children. If swallowed, get medical help or contact a Poison Control Center right away.

Keep the lid of this container tightly closed.

Inactive ingredients

Carpobol 90, T.E.A Triethanolamine, Glycerin

Directions

- Place enough product on hands to cover all surfaces. Rub hands together until dry.
- Supervise children under 6 years of age when using this product to avoid swallowing.

Other information

- Store between 15-30C (59-86F)
- Avoid freezing and excessive heat above 40C (104F)

Package Label - Principal Display Panel

60 mL NDC:75778-005-60

118 mL NDC:75778-005-11

236 mL NDC:75778-005-23

473 mL NDC:75778-005-47